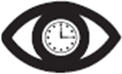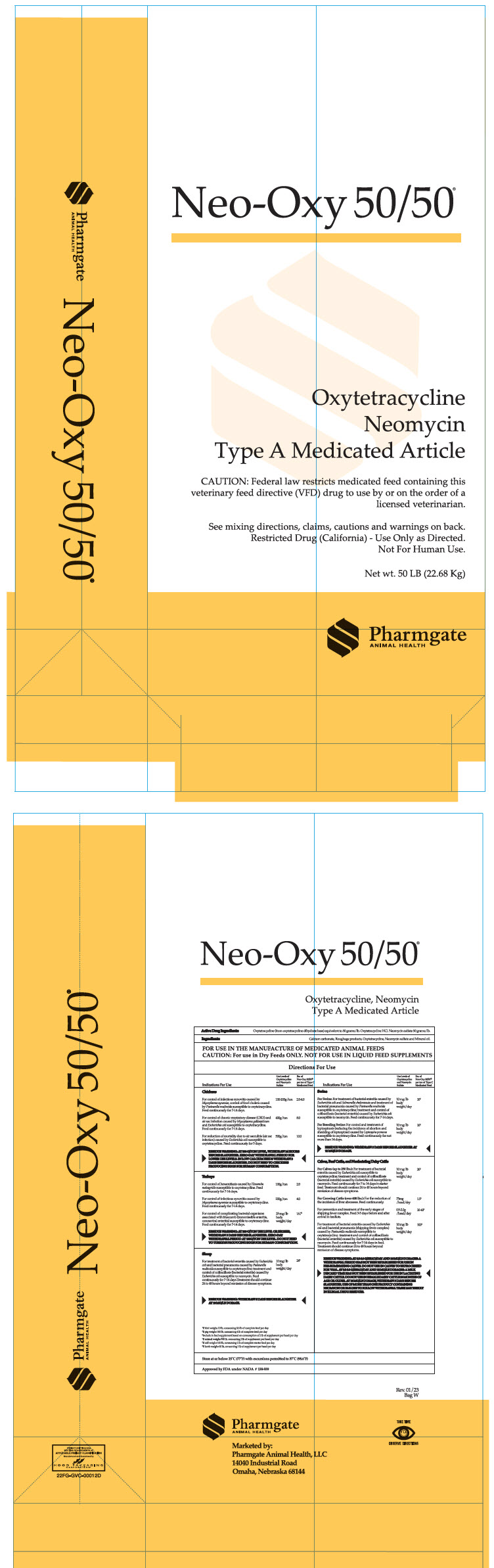 DRUG LABEL: Neo-Oxy 50/50
NDC: 51429-055 | Form: POWDER
Manufacturer: Pharmgate Animal Health
Category: animal | Type: VFD TYPE A MEDICATED ARTICLE ANIMAL DRUG LABEL
Date: 20260107

ACTIVE INGREDIENTS: Oxytetracycline 110 g/1 kg; Neomycin Sulfate 110 g/1 kg
INACTIVE INGREDIENTS: Calcium Carbonate; Mineral Oil

Neo-Oxy 50/50®

Oxytetracycline, Neomycin
Type A Medicated Article

DESCRIPTION

Active Drug Ingredients: Oxytetracycline (from oxytetracycline dihydrate base) equivalent to 50 grams/lb. Oxytetracycline HCl. Neomycin sulfate 50 grams/lb.

Ingredients: Calcium carbonate, Roughage products, Oxytetracycline, Neomycin sulfate and Mineral oil.

INDICATIONS AND USAGE

FOR USE IN THE MANUFACTURE OF MEDICATED ANIMAL FEEDS

PRECAUTIONS

CAUTION: For Use in Dry Feeds ONLY. NOT FOR USE IN LIQUID FEED SUPPLEMENTS

Directions For Use

Indications For Use | Use Level of Oxytetracycline and Neomycin Sulfate | lbs. of Neo-Oxy 50/50® per ton of Type C Medicated Feed
Chickens
For control of infectious synovitis caused by Mycoplasma synoviae, control of fowl cholera caused by Pasteurella multocida susceptible to oxytetracycline. Feed continuously for 7-14 days. | 100-200g/ton | 2.0-4.0
For control of chronic respiratory disease (CRD) and air sac infection caused by Mycoplasma gallisepticum and Escherichia coli susceptible to oxytetracycline. Feed continuously for 7-14 days. | 400g/ton | 8.0
For reduction of mortality due to air sacculitis (air sac infection) caused by Escherichia coli susceptible to oxytetracycline. Feed continuously for 5 days. | 500g/ton | 10.0
RESIDUE WARNING: AT 500 G/TON LEVEL, WITHDRAW 24 HOURS BEFORE SLAUGHTER. ZERO-DAY WITHDRAWAL PERIOD FOR LOWER USE LEVELS. IN LOW CALCIUM FEEDS WITHDRAW 3 DAYS BEFORE SLAUGHTER. DO NOT FEED TO CHICKENS PRODUCING EGGS FOR HUMAN CONSUMPTION.
Turkeys
For control of hexamitiasis caused by Hexamita meleagridis susceptible to oxytetracycline. Feed continuously for 7-14 days. | 100g/ton | 2.0
For control of infectious synovitis caused by Mycoplasma synoviae susceptible to oxytetracycline. Feed continuously for 7-14 days. | 200g/ton | 4.0
For control of complicating bacterial organisms associated with bluecomb (transmissible enteritis, coronaviral enteritis) susceptible to oxytetracycline. Feed continuously for 7-14 days. | 25 mg/lb body weight/day | 16.7 [If bird weighs 10 lb, consuming 0.6 lb of complete feed per day]
RESIDUE WARNING: AT 200 G/TON USE LEVEL OR HIGHER, WITHDRAW 5 DAYS BEFORE SLAUGHTER. ZERO-DAY WITHDRAWAL PERIOD AT 100G/TON USE LEVELS. DO NOT FEED TO TURKEYS PRODUCING EGGS FOR HUMAN CONSUMPTION.
Sheep
For treatment of bacterial enteritis caused by Escherichia coli and bacterial pneumonia caused by Pasteurella multocida susceptible to oxytetracycline; treatment and control of colibacillosis (bacterial enteritis) caused by Escherichia coli susceptible to neomycin. Feed continuously for 7-14 days. Treatment should continue 24 to 48 hours beyond remission of disease symptoms. | 10 mg/lb body weight/day | 24 [If lamb weighs 60 lb, consuming 1 lb of supplement per head per day]
RESIDUE WARNING: WITHDRAW 5 DAYS BEFORE SLAUGHTER AT 10 MG/LB DOSAGE.
Swine
For Swine: For treatment of bacterial enteritis caused by Escherichia coli and Salmonella choleraesuis and treatment of bacterial pneumonia caused by Pasteurella multocida susceptible to oxytetracycline; treatment and control of colibacillosis (bacterial enteritis) caused by Escherichia coli susceptible to neomycin. Feed continuously for 7-14 days. | 10 mg/lb body weight/day | 10 [If pig weighs 100 lb, consuming 4 lb of complete feed per day]
For Breeding Swine: For control and treatment of leptospirosis (reducing the incidence of abortion and shedding of leptospirae) caused by Leptospira pomona susceptible to oxytetracycline. Feed continuously for not more than 14 days. | 10 mg/lb body weight/day | 10
RESIDUE WARNING: WITHDRAW 5 DAYS BEFORE SLAUGHTER AT 10 MG/LB DOSAGE.
Calves, Beef Cattle, and Nonlactating Dairy Cattle
For Calves (up to 250 lbs.): For treatment of bacterial enteritis caused by Escherichia coli susceptible to oxytetracycline; treatment and control of colibacillosis (bacterial enteritis) caused by Escherichia coli susceptible to neomycin. Feed continuously for 7 to 14 days in starter feed. Treatment should continue 24 to 48 hours beyond remission of disease symptoms. | 10 mg/lb body weight/day | 20 [If calf weighs 100 lb, consuming 2 lb of complete starter feed per day]
For Growing Cattle (over 400 lbs.): For the reduction of the incidence of liver abscesses. Feed continuously. | 75mg/head/day | 1.5 [Include in feed supplement based on consumption of 2 lb of supplement per head per day]
For prevention and treatment of the early stages of shipping fever complex. Feed 3-5 days before and after arrival in feedlots. | 0.5-2.0g/head/day | 10-40
For treatment of bacterial enteritis caused by Escherichia coli and bacterial pneumonia (shipping fever complex) caused by Pasteurella multocida susceptible to oxytetracycline; treatment and control of colibacillosis (bacterial enteritis) caused by Escherichia coli susceptible to neomycin. Feed continuously for 7-14 days in feed. Treatment should continue 24 to 48 hours beyond remission of disease symptoms. | 10 mg/lb body weight/day | 100 [If animal weighs 500 lb, consuming 2 lb of supplement per head per day]
RESIDUE WARNING: AT 0.5-2.0 G/HEAD/DAY AND 10 MG/LB DOSAGES: A WITHDRAWAL PERIOD HAS NOT BEEN ESTABLISHED FOR USE IN PRE-RUMINATING CALVES. DO NOT USE IN CALVES TO BE PROCESSED FOR VEAL. AT 0.5-2.0 G/HEAD/DAY AND 10 MG/LB DOSAGES: A MILK DISCARD TIME HAS NOT BEEN ESTABLISHED FOR USE IN LACTATING DAIRY CATTLE. DO NOT USE IN FEMALE DAIRY CATTLE 20 MONTHS OF AGE OR OLDER. AT 10 MG/LB DOSAGE, WITHDRAW 5 DAYS BEFORE SLAUGHTER. USE OF MORE THAN ONE PRODUCT CONTAINING NEOMYCIN OR FAILURE TO FOLLOW WITHDRAWAL TIMES MAY RESULT IN ILLEGAL DRUG RESIDUES.
Store at or below 25°C (77°F) with excursions permitted to 37°C (98.6°F) Approved by FDA under NADA # 138-939

Net wt. 50 LB (22.68 Kg)

Marketed by:
Pharmgate Animal Health, LLC
14040 Industrial Road
Omaha, NE 68144

Take Time |  | Observe Directions

PRINCIPAL DISPLAY PANEL - 22.68 Kg Bag Label

Neo-Oxy 50/50®

Oxytetracycline
Neomycin
Type A Medicated Article

CAUTION: Federal law restricts medicated feed containing this
veterinary feed directive (VFD) drug to use by or on the order of a
licensed veterinarian.

See mixing directions, claims, cautions and warnings on back.
Restricted Drug (California) - Use Only as Directed.
Not For Human Use.

Net wt. 50 LB (22.68 Kg)

Pharmgate
ANIMAL HEALTH